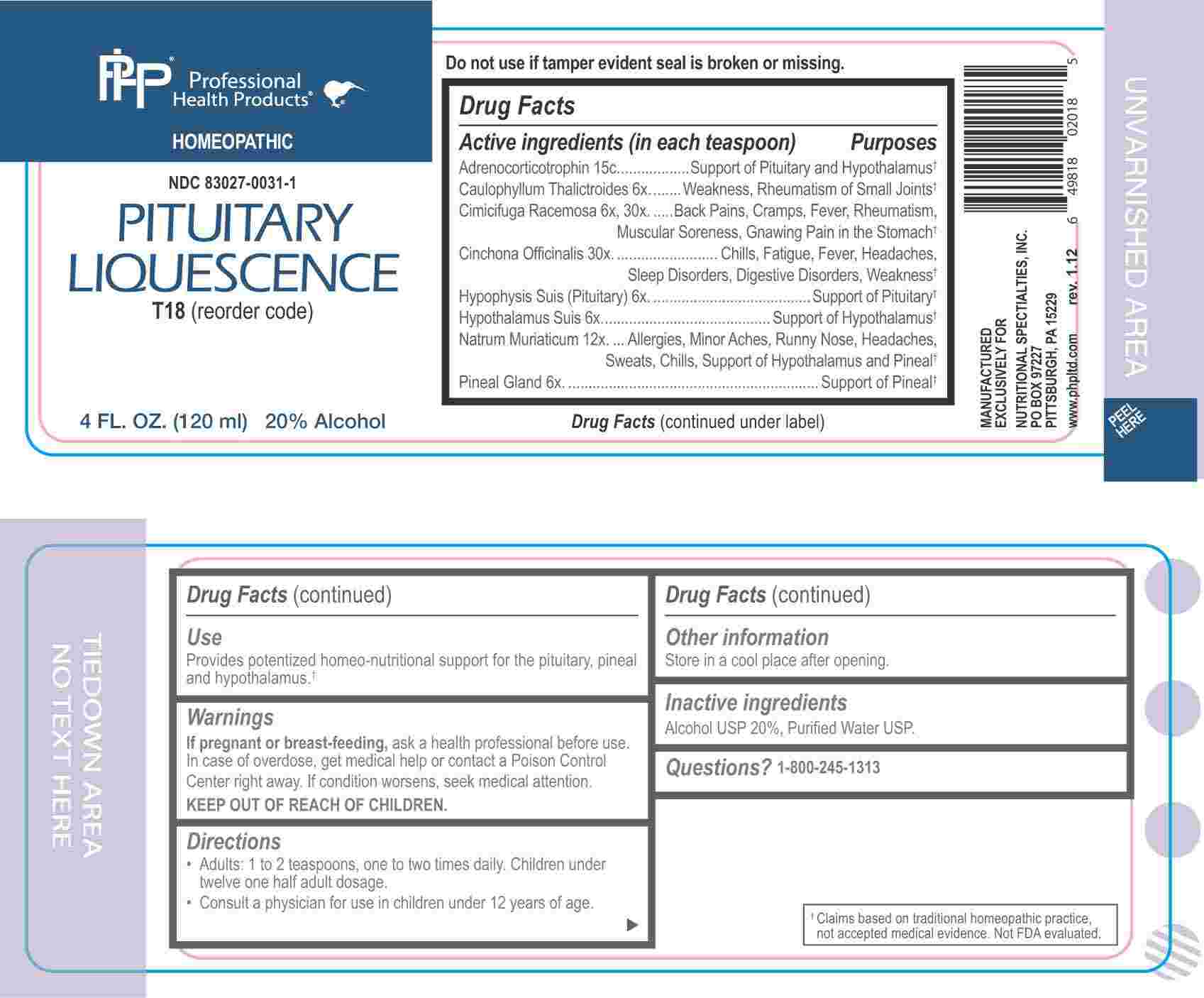 DRUG LABEL: Pituitary Liquescence
NDC: 83027-0031 | Form: LIQUID
Manufacturer: Nutritional Specialties, Inc.
Category: homeopathic | Type: HUMAN OTC DRUG LABEL
Date: 20250320

ACTIVE INGREDIENTS: CAULOPHYLLUM THALICTROIDES ROOT 6 [hp_X]/1 mL; SUS SCROFA PITUITARY GLAND 6 [hp_X]/1 mL; SUS SCROFA HYPOTHALAMUS 6 [hp_X]/1 mL; SUS SCROFA PINEAL GLAND 6 [hp_X]/1 mL; BLACK COHOSH 6 [hp_X]/1 mL; SODIUM CHLORIDE 12 [hp_X]/1 mL; CINCHONA OFFICINALIS BARK 30 [hp_X]/1 mL; CORTICOTROPIN 15 [hp_C]/1 mL
INACTIVE INGREDIENTS: WATER; ALCOHOL

DRUG FACTS:

ACTIVE INGREDIENTS:

Adrenocorticotrophin 15C, Caulophyllum Thalictroides 6X, Cimicifuga Racemosa 6X, Cinchona Officinalis 30X, Hypophysis Suis (Pituitary) 6X, Hypothalamus Suis 6X, Natrum Muriaticum 12X, Pineal Gland (Suis) 6X, 30X.

PURPOSE:

Adrenocorticotrophin – Support of Pituitary and Hypothalamus,† Caulophyllum Thalictroides – Weakness, Rheumatism of Small Joints,† Cimicifuga Racemosa – Back Pains, Cramps, Fever, Rheumatism, Muscular Soreness, Gnawing Pain in the Stomach,† Cinchona Officinalis – Chills, Fatigue, Fever, Headaches, Sleep Disorders, Digestive Disorders, Weakness,† Hypophysis Suis (Pituitary) – Support of Pituitary,† Hypothalamus Suis – Support of Hypothalamus,† Natrum Muriaticum – Allergies, Minor Aches, Runny Nose, Headaches, Sweats, Chills, Support of Hypothalamus and Pineal,† Pineal Gland – Support of Pineal†

†Claims based on traditional homeopathic practice, not accepted medical evidence. Not FDA evaluated.

USES:

Provides potentized homeo-nutritional support for the pituitary, pineal and hypothalamus.†

†Claims based on traditional homeopathic practice, not accepted medical evidence. Not FDA evaluated.

WARNINGS:

If pregnant or breast-feeding, ask a health professional before use.

In case of overdose, get medical help or contact a Poison Control Center right away.

If condition worsens, seek medical attention.

KEEP OUT OF REACH OF CHILDREN

Do not use if tamper evident seal is broken or missing.

Store in a cool place after opening

KEEP OUT OF REACH OF CHILDREN:

In case of overdose, get medical help or contact a Poison Control Center right away.

DIRECTIONS:

• Adults: 1 to 2 teaspoons, one to two times daily. Children under twelve one half adult dosage.

Consult a physician for use in children under 12 years of age.

INACTIVE INGREDIENTS:

Alcohol USP 20%, Purified Water USP.

QUESTIONS:

MANUFACTURED EXCLUSIVELY FOR

NUTRITIONAL SPECIALTIES, INC.

PO BOX 97227

PITTSBURG, PA 15229

www.phpltd.com

1-800-245-1313

PACKAGE LABEL DISPLAY:

Professional

Health Products

HOMEOPATHIC

NDC 83027-0031-1

PITUITARY

LIQUESCENCE

4 FL. OZ (120 ml)